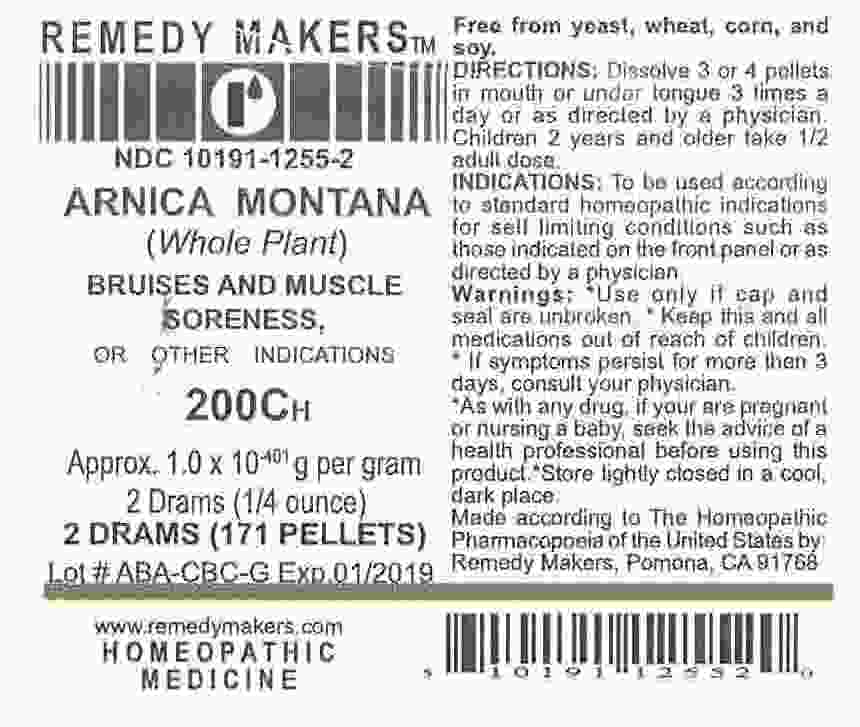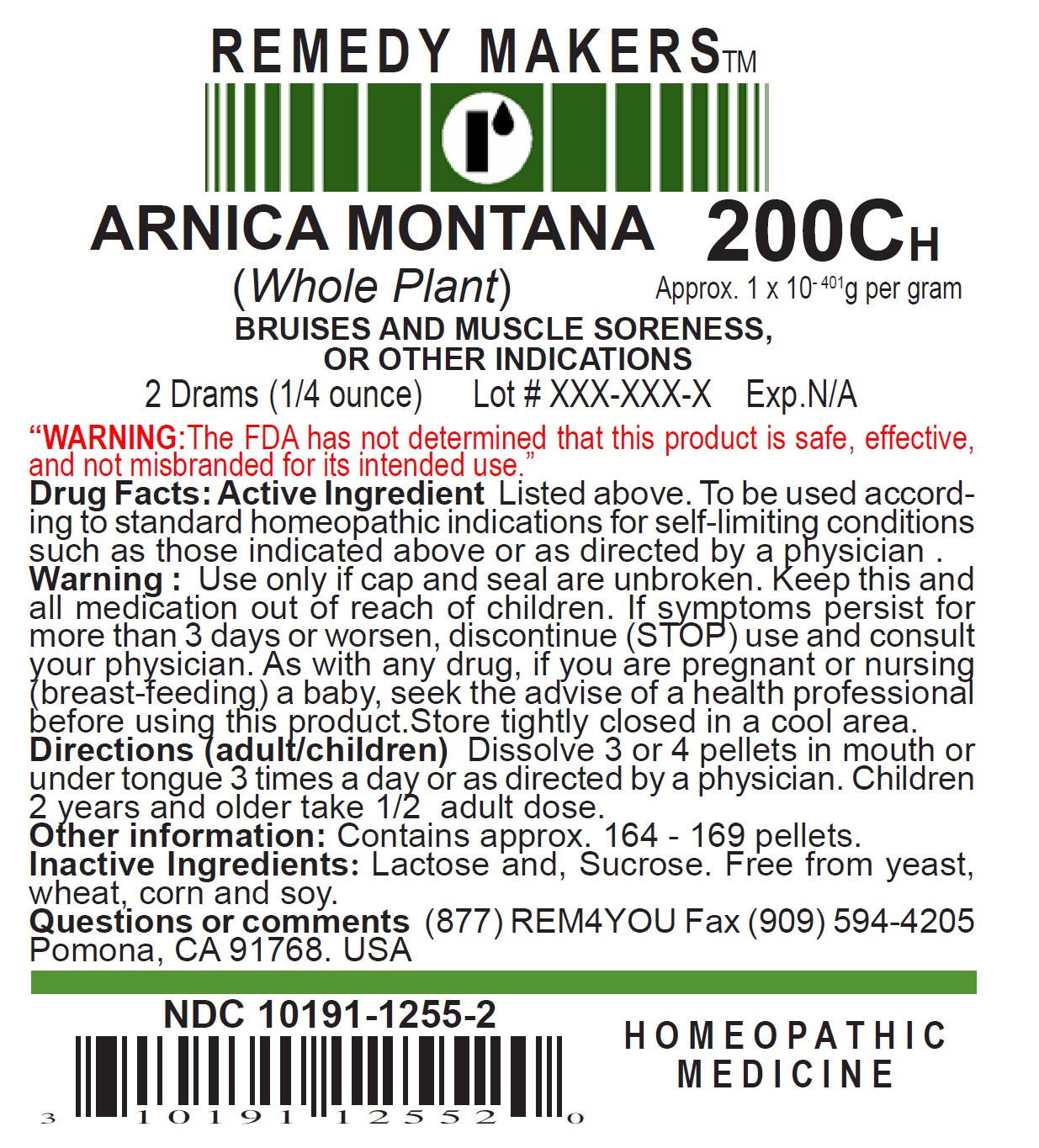 DRUG LABEL: ARNICA MONTANA (Whole Plant)
NDC: 10191-1255 | Form: PELLET
Manufacturer: Remedy Makers
Category: homeopathic | Type: HUMAN OTC DRUG LABEL
Date: 20230323

ACTIVE INGREDIENTS: ARNICA MONTANA 20 [hp_M]/1 1
INACTIVE INGREDIENTS: SUCROSE; LACTOSE, UNSPECIFIED FORM

ARNICA MONTANA 200C (Whole Plant)

ACTIVE INGREDIENT

ARNICA MONTANA 200C

(WHOLE PLANT)

PURPOSE

BRUISES AND MUSCLE SORENESS, OR OTHER INDICATIONS

WARNING:

"The FDA has not determined that this product is safe, effective and not misbranded for its intended use."

INDICATIONS AND USAGE

To be used according to standard homeopathic indications for self-limiting conditions such as those indicated above or as directed by a physician.

KEEP OUT OF REACH OF CHILDREN

Keep this and all medication out of reach of children.

Warning:

Use only if cap and seal are unbroken. If symptoms persist for more than 3 days or worsen, discontinue (STOP) use and consult your physician. As with any drug, if you are pregnant or nursing (breast-feeding) a baby, seek the advise of a health professional before using this product. Store tightly closed in a cool area.

Directions (adult/children)

Dissolve 3 or 4 pellets in mouth or under tongue 3 times a day or as directed by a physician. Children 2 years and older take 1/2 adult dose.

Other Information:

Contains approx. 164-169 pellets.

Inactive Ingredients:

Lactose and Sucrose. Free from yeast, wheat, corn and soy.

Questions or comments

(877) REM4YOU Fax (909) 594-4205 Pomona, CA 91768. USA

INDICATIONS AND USAGE

Free from yeast, wheat, corn, and soy.
DIRECTIONS: Dissolve 3 or 4 pellets
in mouth or under tongue 3 times a day or as directed by a physician.
Children 2 years and older take 1/2
adult dose.
INDICATIONS: To be used according
to standard homeopathic indications
for self limiting conditions such as
those indicated on the front panel or as directed by a physician.
Warnings: *Use only if cap and
seal are unbroken. * Keep this and all medications out of reach of children.
* If symptoms persist for more then 3
days, consult your physician.
*As with any drug, if your are pregnant or nursing a baby, seek the advice of a
health professional before using this product.*Store tightly closed in a cool, dark place.
Made according to The Homeopathic Pharmacopoeia of the United States by: Remedy Makers, Pomona, CA 91768